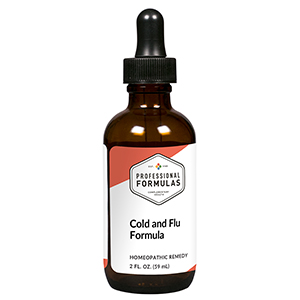 DRUG LABEL: Cold and Flu Formula
NDC: 63083-2109 | Form: LIQUID
Manufacturer: Professional Complementary Health Formulas
Category: homeopathic | Type: HUMAN OTC DRUG LABEL
Date: 20190815

ACTIVE INGREDIENTS: GINGER 2 [hp_X]/59 mL; MENTHA PULEGIUM WHOLE 3 [hp_X]/59 mL; LONICERA HYPOGLAUCA FLOWER 3 [hp_X]/59 mL; STACHYURUS CHINENSIS WHOLE 3 [hp_X]/59 mL; FORSYTHIA SUSPENSA FRUIT 3 [hp_X]/59 mL; ARCTIUM LAPPA FRUIT 3 [hp_X]/59 mL; ASTRAGALUS PROPINQUUS ROOT 6 [hp_X]/59 mL; BOS TAURUS PLACENTA 6 [hp_X]/59 mL
INACTIVE INGREDIENTS: ALCOHOL; WATER

C109

ACTIVE INGREDIENTS

Gan-Jiang 2X
Bo-He 3X
Jin-Yin-Hua 3X
Jing-Jie 3X
Lian-Jiao 3X
Niu-Bang-Zi 3X
Huang-Qi 6X
Zi-He-Che 6X

QUESTIONS

Professional Formulas

PO Box 2034 Lake Oswego, OR 97035

INDICATIONS

For the temporary relief of cough, shortness of breath, congestion, low-grade fever, sore throat, or weakness.*

PURPOSE

*Claims based on traditional homeopathic practice, not accepted medical evidence. Not FDA evaluated.

WARNINGS

Persistent symptoms may be a sign of a serious condition. If symptoms persist or are accompanied by a fever, rash, or persistent headache, consult a doctor. Keep out of the reach of children. In case of overdose, get medical help or contact a poison control center right away. If pregnant or breastfeeding, ask a healthcare professional before use.

Keep out of the reach of children.

PREGNANCY OR BREAST FEEDING

If pregnant or breastfeeding, ask a healthcare professional before use.

DIRECTIONS

Place drops under tongue 30 minutes before/after meals. Adults and children 12 years and over: Take 10 drops up to 3 times per day for up to 6 weeks. For immediate onset of symptoms, take 10 to 15 drops every 15 minutes up to 3 hours. For less severe symptoms, take 10-15 drops hourly up to 8 hours. Consult a physician for use in children under 12 years of age.

OTHER INFORMATION

Tamper resistant. If seal is broken, do not use. After opening, close container tightly and store at room temperature away from heat.

INACTIVE INGREDIENTS

20% ethanol, purified water.

LABEL

Est 1985

Professional Formulas

Complementary Health

Cold and Flu Formula

Homeopathic Remedy

2 FL. OZ. (59 mL)